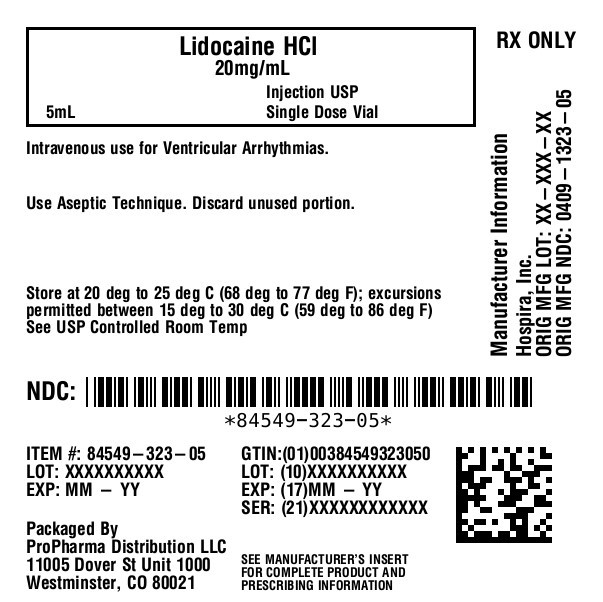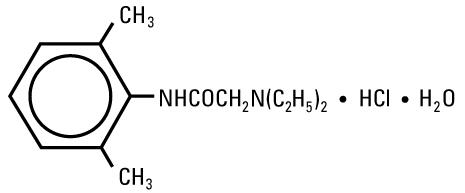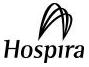 DRUG LABEL: Lidocaine Hydrochloride
NDC: 84549-323 | Form: INJECTION, SOLUTION
Manufacturer: ProPharma Distribution
Category: prescription | Type: HUMAN PRESCRIPTION DRUG LABEL
Date: 20251218

ACTIVE INGREDIENTS: LIDOCAINE HYDROCHLORIDE 20 mg/1 mL
INACTIVE INGREDIENTS: SODIUM HYDROXIDE; HYDROCHLORIC ACID; SODIUM CHLORIDE

LIDOCAINE
HYDROCHLORIDE
INJECTION, USP

AQUEOUS SOLUTIONS FOR

ACUTE MANAGEMENT OF

VENTRICULAR ARRHYTHMIAS

Ansyr®Plastic Syringe

LifeShield®Abboject®Syringe

Rx only

DESCRIPTION

Lidocaine Hydrochloride Injection, USP is a sterile, nonpyrogenic solution of an antiarrhythmic agent administered intravenously by either direct injection or continuous infusion. It is available in various concentrations with the following characteristics:

 | Volume (Total Lidocaine HCl) | Lidocaine Hydrochloride (mg/mL) | pH
For Direct Intravenous Injection:
 | 5 mL (100 mg) | 20 | 5.0 to 7.0
Single-dose:
 | 5 mL (50 mg) | 10 | 5.0 to 7.0

May contain sodium hydroxide and/or hydrochloric acid for pH adjustment. Injections containing 10 mg/mL (1%) contain sodium chloride 7 mg and injections containing 20 mg/mL (2%) lidocaine hydrochloride contain sodium chloride 6 mg to adjust tonicity. Single-dose solutions contain no preservative and unused portions must be discarded after use.

Lidocaine Hydrochloride, USP is chemically designated 2-(Diethylamino)-2',6'-acetoxylidide monohydrochloride monohydrate, a white powder freely soluble in water. The molecular formula is C14H22N2O • HCl • H2O. The molecular weight is 288.82. It has the following structural formula:

The semi-rigid vial used for the plastic vials is fabricated from a specially formulated polyolefin. It is a copolymer of ethylene and propylene. The safety of the plastic has been confirmed by tests in animals according to USP biological standards for plastic containers. The container requires no vapor barrier to maintain the proper drug concentration.

The plastic syringe is molded from a specially formulated polypropylene. Water permeates from inside the container at an extremely slow rate which will have an insignificant effect on solution concentration over the expected shelf life. Solutions in contact with the plastic container may leach out certain chemical components from the plastic in very small amounts; however, biological testing was supportive of the safety of the syringe material.

CLINICAL PHARMACOLOGY

Mechanism of Action and Electrophysiology:

Studies of the effects of therapeutic concentrations of lidocaine on the electrophysiological properties of mammalian Purkinje fibers have shown that lidocaine attenuates phase 4 diastolic depolarization, decreases automaticity and causes a decrease or no change in excitability and membrane responsiveness. Action potential duration and effective refractory period of Purkinje fibers are decreased while the ratio of effective refractory period to action potential duration is increased. Action potential duration and effective refractory period of ventricular muscle are also decreased. Effective refractory period of the AV node may increase, decrease or remain unchanged and atrial effective refractory period is unchanged. Lidocaine raises the ventricular fibrillation threshold. No significant interactions between lidocaine and the autonomic nervous system have been described and consequently lidocaine has little or no effect on autonomic tone.

Clinical electrophysiological studies with lidocaine have demonstrated no change in sinus node recovery time or sinoatrial conduction time. AV nodal conduction time is unchanged or shortened and His-Purkinje conduction time is unchanged.

Hemodynamics:

At therapeutic doses, lidocaine has minimal hemodynamic effects in normal subjects and in patients with heart disease. Lidocaine has been shown to cause no, or minimal decrease in ventricular contractility, cardiac output, arterial pressure or heart rate.

Pharmacokinetics and Metabolism:

Lidocaine is rapidly metabolized by the liver and less than 10% of a dose is excreted unchanged in the urine. Oxidative N-dealkylation, a major pathway of metabolism, results in the metabolites monoethylglycinexylidide and glycinexylidide. The pharmacological/toxicological activities of these metabolites are similar to but less potent than lidocaine. The primary metabolite in urine is a conjugate of 4-hydroxy-2, 6-dimethylaniline.

The elimination half-life of lidocaine following an intravenous bolus injection is typically 1.5 to 2 hours. There are data that indicate that the half-life may be 3 hours or longer following infusions of greater than 24 hours.

Because of the rapid rate at which lidocaine is metabolized, any condition that alters liver function, including changes in liver blood flow, which could result from severe congestive heart failure or shock may alter lidocaine kinetics. The half-life may be two-fold or more greater in patients with liver dysfunction. Renal dysfunction does not affect lidocaine kinetics, but may increase the accumulation of metabolites.

Therapeutic effects of lidocaine are generally associated with plasma levels of 6 to 25 μmole/L (1.5 to 6 mcg free base per mL). The blood to plasma distribution ratio is approximately 0.84. Objective adverse manifestations become increasingly apparent with increasing plasma levels above 6 mcg free base per mL.

The plasma protein binding of lidocaine is dependent on drug concentration and the fraction bound decreases with increasing concentration. At concentrations of 1 to 4 mcg free base per mL, 60 to 80 percent of lidocaine is protein bound. In addition to lidocaine concentration, the binding is dependent on the plasma concentration of the α-1-acid glycoprotein.

Lidocaine readily crosses the placental and blood-brain barriers. Dialysis has negligible effects on the kinetics of lidocaine.

INDICATIONS AND USAGE

Lidocaine hydrochloride injection administered intravenously or intramuscularly, is specifically indicated in the acute management of ventricular arrhythmias such as those occurring in relation to acute myocardial infarction, or during cardiac manipulation, such as cardiac surgery.

CONTRAINDICATIONS

Lidocaine hydrochloride is contraindicated in patients with a known history of hypersensitivity to local anesthetics of the amide type. Lidocaine hydrochloride should not be used in patients with Stokes-Adams syndrome, Wolff-Parkinson-White syndrome or with severe degrees of sinoatrial, atrioventricular or intraventricular block in the absence of an artificial pacemaker.

WARNINGS

IN ORDER TO MANAGE POSSIBLE ADVERSE REACTIONS, RESUSCITATIVE EQUIPMENT, OXYGEN AND OTHER RESUSCITATIVE DRUGS SHOULD BE IMMEDIATELY AVAILABLE WHEN LIDOCAINE HYDROCHLORIDE INJECTION IS USED.

Systemic toxicity may result in manifestations of central nervous system depression (sedation) or irritability (twitching), which may progress to frank convulsions accompanied by respiratory depression and/or arrest. Early recognition of premonitory signs, assurance of adequate oxygenation and, where necessary, establishment of artificial airway with ventilatory support are essential to management of this problem. Should convulsions persist despite ventilatory therapy with oxygen, smallincrements of anticonvulsant drugs may be used intravenously. Examples of such agents include benzodiazepines (e.g., diazepam), ultrashort-acting barbiturates (e.g., thiopental or thiamylal) or a short-acting barbiturate (e.g., pentobarbital or secobarbital). If the patient is under anesthesia, a short-acting muscle relaxant (e.g., succinylcholine) may be used. Longer acting drugs should be used only when recurrent convulsions are evidenced.

Should circulatory depression occur, vasopressors may be used.

Constant electrocardiographic monitoring is essential to the proper administration of lidocaine hydrochloride. Signs of excessive depression of cardiac electrical activity such as sinus node dysfunction, prolongation of the P-R interval and QRS complex or the appearance or aggravation of arrhythmias, should be followed by flow adjustment and, if necessary, prompt cessation of the intravenous infusion of this agent. Occasionally, acceleration of ventricular rate may occur when lidocaine hydrochloride is administered to patients with atrial flutter or fibrillation.

PRECAUTIONS

1. General:

Caution should be employed in the use of lidocaine hydrochloride in patients with severe liver or kidney disease because accumulation of the drug or metabolites may occur.

Lidocaine Hydrochloride Injection, USP should be used with caution in the treatment of patients with hypovolemia, severe congestive heart failure, shock and all forms of heart block. In patients with sinus bradycardia or incomplete heart block, the administration of lidocaine hydrochloride intravenously for the elimination of ventricular ectopic beats without prior acceleration in heart rate (e.g., by atropine, isoproterenol or electric pacing) may promote more frequent and serious ventricular arrhythmias or complete heart block (see CONTRAINDICATIONS).

Dosage should be reduced for pediatric patients and for debilitated and/or elderly patients, commensurate with their age and physical status.

The safety of amide local anesthetic agents in patients with genetic predisposition of malignant hyperthermia has not been fully assessed; therefore, lidocaine should be used with caution in such patients.

In hospital environments where drugs known to be triggering agents for malignant hyperthermia (fulminant hypermetabolism) are administered, it is suggested that a standard protocol for management should be available.

It is not known whether lidocaine may trigger this reaction; however, large doses resulting in significant plasma concentrations, as may be achieved by intravenous infusion, pose potential risk to these individuals. Recognition of early unexplained signs of tachycardia, tachypnea, labile blood pressure and metabolic acidosis may precede temperature elevation. Successful outcome is dependent on early diagnosis, prompt discontinuance of the triggering agent and institution of treatment including oxygen therapy, supportive measures and dantrolene (for details see dantrolene package insert).

2. Patient Information:

The patient should be advised of the possible occurrence of the experiences listed under ADVERSE REACTIONS.

3. Laboratory Tests:

None known.

4. Drug Interactions:

Lidocaine Hydrochloride Injection, USP should be used with caution in patients with digitalis toxicity accompanied by atrioventricular block. Concomitant use of beta-blocking agents or cimetidine may reduce hepatic blood flow and thereby reduce lidocaine clearance. The concomitant use of these two agents may cause an increased incidence of adverse reactions, including central nervous system adverse reactions such as seizure.

Lidocaine and tocainide are pharmacodynamically similar.

5. Carcinogenesis, Mutagenesis, Impairment of Fertility:

Long term studies in animals to evaluate the carcinogenic and mutagenic potential or the effect on fertility of lidocaine HCl have not been conducted.

6. Pregnancy:

Teratogenic Effects:Reproduction studies have been performed in rats at doses up to 6.6 times the maximum human doses and have revealed no significant findings. There are, however, no adequate and well-controlled studies in pregnant women. Because animal reproduction studies are not always predictive of human response, this drug should be used during pregnancy only if clearly needed.

7. Labor and Delivery:

The effects of lidocaine HCl on the mother and the fetus, when used in the management of cardiac arrhythmias during labor and delivery are not known. Lidocaine readily crosses the placental barrier.

8. Nursing Mothers:

It is not known whether this drug is excreted in human milk. Because many drugs are excreted in human milk, caution should be exercised when lidocaine is administered to a nursing woman.

9. Pediatric Use:

Controlled clinical studies have not been conducted in the pediatric population to establish safety and efficacy in this population (see DOSAGE AND ADMINISTRATION).

ADVERSE REACTIONS

Adverse experiences following the administration of lidocaine are similar in nature to those observed with other amide local anesthetic agents. Adverse experiences may result from high plasma levels caused by excessive dosage or may result from a hypersensitivity, idiosyncrasy or diminished tolerance on the part of the patient. Serious adverse experiences are generally systemic in nature. The following types are those most commonly reported. The adverse experiences under Central Nervous System and Cardiovascular System are listed, in general, in a progression from mild to severe.

1. Central Nervous System:CNS reactions are excitatory and/or depressant and may be characterized by light-headedness, nervousness, apprehension, euphoria, confusion, dizziness, drowsiness, tinnitus, blurred or double vision, vomiting, sensations of heat, cold or numbness, twitching, tremors, convulsions, unconsciousness, respiratory depression and arrest. The excitatory reactions may be very brief or may not occur at all, in which case, the first manifestation of toxicity may be drowsiness, merging into unconsciousness and respiratory arrest.
2. Cardiovascular System:Cardiovascular reactions are usually depressant in nature and are characterized by bradycardia, hypotension and cardiovascular collapse, which may lead to cardiac arrest.
3. Allergic reactions as a result of sensitivity to lidocaine are extremely rare and, if they occur, should be managed by conventional means.
4. Neurologic:There have been reported cases of permanent injury to extraocular muscles requiring surgical repair following retrobulbar administration.

DRUG ABUSE AND DEPENDENCE

Although specific studies have not been conducted, lidocaine HCl has been used clinically without evidence of abuse of this drug or of psychological or physical dependence as a result of its use.

OVERDOSAGE

Overdosage of lidocaine HCl usually results in signs of central nervous system or cardiovascular toxicity (see ADVERSE REACTIONS).

Should convulsions or signs of respiratory depression and arrest develop, the patency of the airway and adequacy of ventilation must be assured immediately. Should convulsions persist despite ventilatory therapy with oxygen, small increments of anticonvulsive agents may be given intravenously. Examples of such agents include a benzodiazepine (e.g., diazepam), an ultrashort-acting barbiturate (e.g., thiopental or thiamylal) or a short-acting barbiturate (e.g., pentobarbital or secobarbital). If the patient is under general anesthesia, a short-acting muscle relaxant (e.g., succinylcholine) may be administered.

Should circulatory depression occur, vasopressors may be used. Should cardiac arrest occur, standard CPR procedures should be instituted.

Dialysis is of negligible value in the treatment of acute overdosage from lidocaine HCl.

DOSAGE AND ADMINISTRATION

Adults:

Single Direct Intravenous Injection (bolus):ONLY THE 5 mL, 50 MG or 100 MG DOSAGE SIZES should be used for direct intravenous injection. The usual dose is 50 to 100 mg of lidocaine hydrochloride (0.70 to 1.4 mg/kg; 0.32 to 0.63 mg/lb) administered intravenously under ECG monitoring. This dose may be administered at the rate of approximately 25 to 50 mg/min (0.35 to 0.70 mg/kg/min; 0.16 to 0.32 mg/lb/min). Sufficient time should be allowed to enable a slow circulation to carry the drug to the site of action. If the initial injection of 50 to 100 mg does not produce a desired response, a second dose may be injected after five minutes. NO MORE THAN 200 TO 300 MG OF LIDOCAINE HYDROCHLORIDE SHOULD BE ADMINISTERED DURING A ONE HOUR PERIOD.

Continuous Intravenous Infusion:Following bolus administration, intravenous infusions of lidocaine hydrochloride may be initiated at the rate of 1 to 4 mg/min of lidocaine hydrochloride (0.014 to 0.057 mg/kg/min; 0.006 to 0.026 mg/lb/min). The rate of intravenous infusions should be reassessed as soon as the patient's basic cardiac rhythm appears to be stable or at the earliest signs of toxicity. It should rarely be necessary to continue intravenous infusions of lidocaine for prolonged periods.

When administering lidocaine hydrochloride (or any potent medication) by continuous intravenous infusion, it is advisable to use a precision volume control I.V. set.

Pediatric:Controlled clinical studies in the pediatric population to establish dosing schedules have not been conducted. The American Heart Association's Standards and Guidelinesrecommends a bolus dose of 1 mg/kg, and an infusion rate of between 20-50 mcg/kg/min for prolonged therapy. When drug clearance is reduced, as in patients with shock, congestive heart failure or cardiac arrest, the infusion rate should not exceed 20 mcg/kg/min.

NOTE: Regarding Prolonged Infusions:There are data that indicate the half-life may be 3 hours or longer following infusions of greater than 24 hours in duration. Do not use if solution is discolored or cloudy.

Parenteral drug products should be inspected visually for particulate matter and discoloration prior to administration whenever solution and container permit.

To prevent needle-stick injuries, needles should not be recapped, purposely bent or broken by hand.

HOW SUPPLIED

Lidocaine Hydrochloride Injection, USP is supplied as follows:

NDC 84549-323-05

Ansyr ® Plastic Syringe

2% (20 mg/mL)

5 mL

Store at 20 to 25° C (68 to 77° F). [See USP Controlled Room Temperature.]

Abboject®is a trademark of the Abbott group of companies.

LIFESHIELD® is the trademark of ICU Medical, Inc. and is used under license.

LAB-1021-3.0

Revised: 04/2018